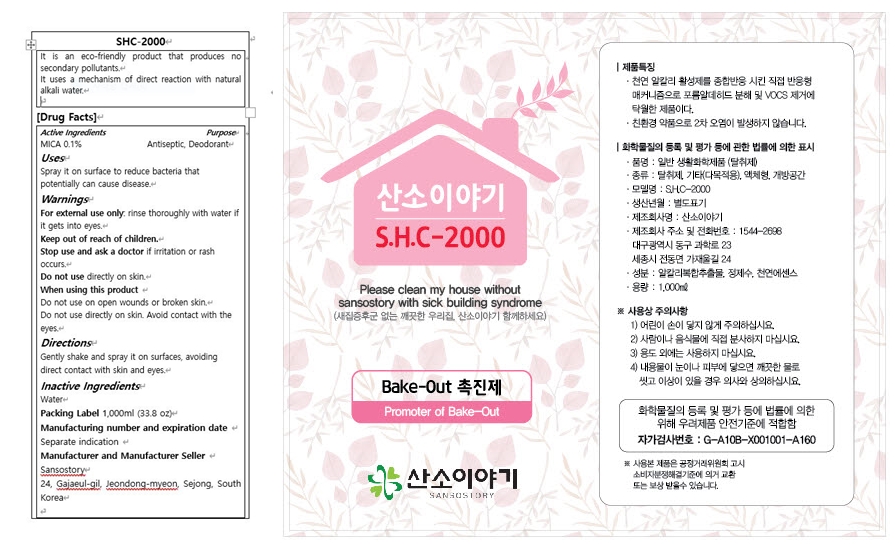 DRUG LABEL: Sansostory SHC2000
NDC: 82346-102 | Form: LIQUID
Manufacturer: sansostory
Category: otc | Type: HUMAN OTC DRUG LABEL
Date: 20221229

ACTIVE INGREDIENTS: MICA 0.1 g/100 g
INACTIVE INGREDIENTS: WATER

82346-102 Sansostory SHC 2000

Active Ingredients

MICA 0.1%

Purpose

Antiseptic, Deodorant

Uses

Spray it on surface to reduce bacteria that potentially can cause disease.

Reduces odor in closed areas.

Warnings

For external use only: rinse thoroughly with water if it gets into eyes.

Warnings

Do not use directly on skin.

Warnings

Keep out of reach of children.

Warnings

Stop use and ask a doctor if irritation or rash ocurs.

Warnings

Do not use on open wounds or broken skin.

Do not use directly on skin.

Avoid contact with the eyes.

Inactive Ingredients

water

Directions

Gently shake and spray it on surfaces, avoiding direct contact with skin and eyes.